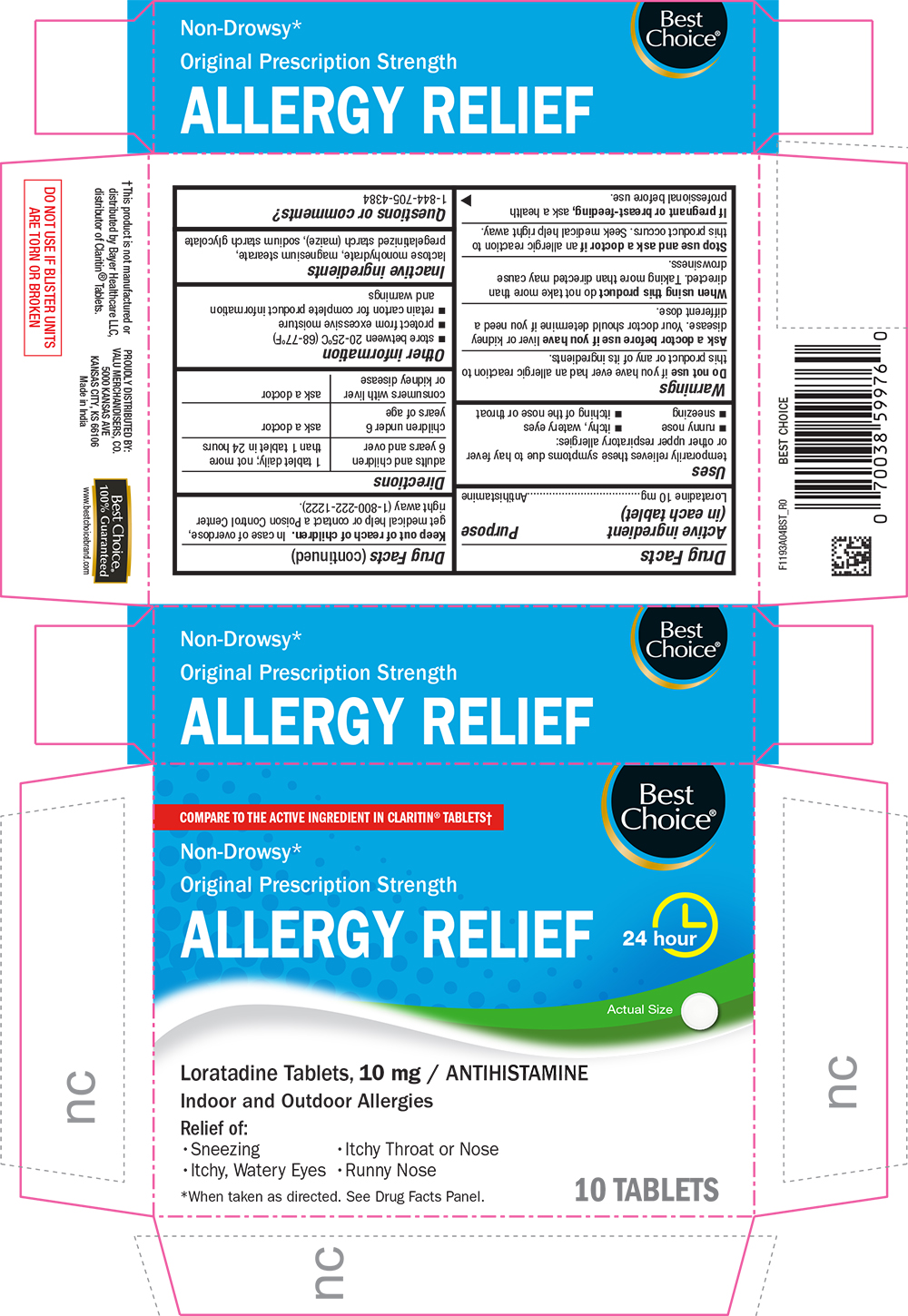 DRUG LABEL: Allergy Relief
NDC: 63941-193 | Form: TABLET
Manufacturer: Valu Merchandisers Company
Category: otc | Type: HUMAN OTC DRUG LABEL
Date: 20251211

ACTIVE INGREDIENTS: LORATADINE 10 mg/1 1
INACTIVE INGREDIENTS: LACTOSE MONOHYDRATE; MAGNESIUM STEARATE; STARCH, CORN; SODIUM STARCH GLYCOLATE TYPE A POTATO

1193A-BST-2020-0909

Drug Facts

Active ingredient (in each tablet)

Loratadine 10 mg

Purpose

Antihistamine

Uses

temporarily relieves these symptoms due to hay fever or other upper respiratory allergies:

- runny nose
- sneezing
- itchy, watery eyes
- itching of the nose or throat

Warnings

Do not use if you have ever had an allergic reaction to this product or any of its ingredients.

Ask a doctor before use if you have liver or kidney disease. Your doctor should determine if you need a different dose.

When using this product do not take more than directed. Taking more than directed may cause drowsiness.

Stop use and ask a doctor if an allergic reaction to this product occurs. Seek medical help right away.

PREGNANCY OR BREAST FEEDING

If pregnant or breast-feeding, ask a health professional before use

Keep out of reach of children.

In case of overdose, get medical help or contact a Poison Control Center right away (1-800-222-1222).

Directions

adults and children 6 years and over | 1 tablet daily; not more than 1 tablet in 24 hours
children under 6 years of age | ask a doctor
consumers with liver or kidney disease | ask a doctor

Other information

- store between 20 to 25°C (68 to 77°F)
- retain carton for complete product information and warnings

Inactive ingredients

lactose monohydrate, magnesium stearate, pregelatinized starch (maize), sodium starch glycolate

Questions or comments?

1-844-705-4384

PRINCIPAL DISPLAY PANEL

Best Choice®

COMPARE TO THE ACTIVE INGREDIENT IN CLARITIN® TABLETS†

Non-Drowsy*

Original Prescription Strength

ALLERGY RELIEF

24 hour

Actual Size

Loratadine Tablets, 10 mg / ANTIHISTAMINE

Indoor and Outdoor Allergies

Relief of:

• Sneezing

• Itchy Throat or Nose

• Itchy, Watery Eyes

• Runny Nose

*When taken as directed. See Drug Facts Panel

10 TABLETS